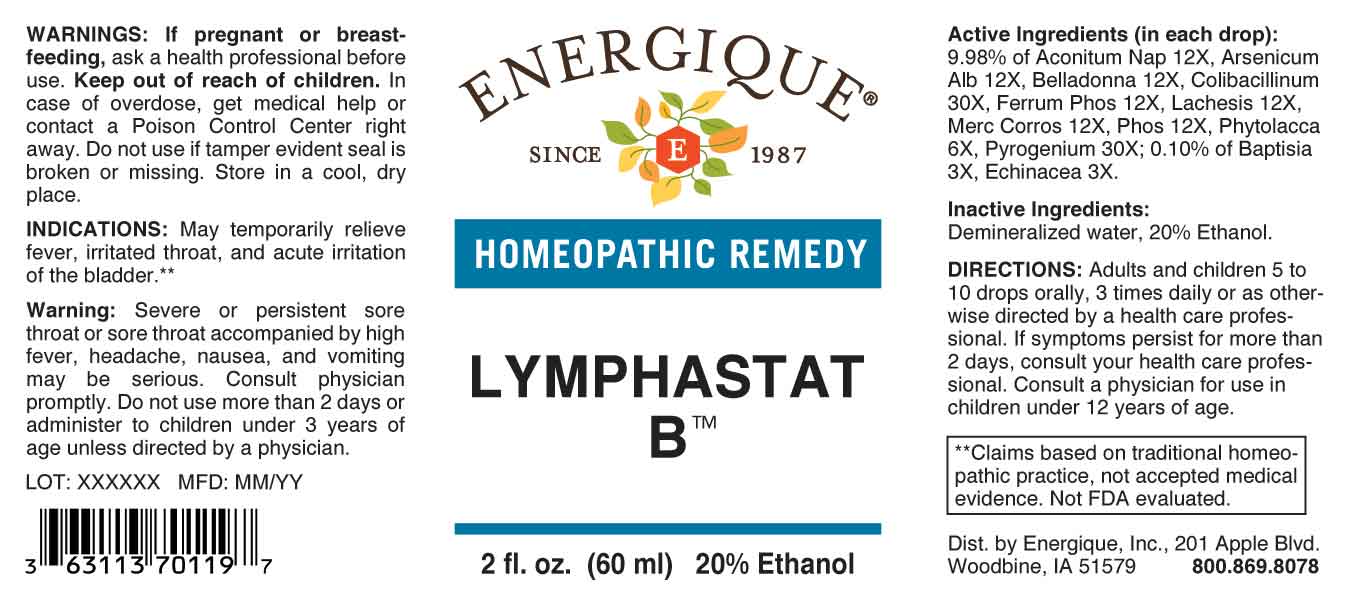 DRUG LABEL: Lymphastat B
NDC: 44911-0682 | Form: LIQUID
Manufacturer: Energique, Inc.
Category: homeopathic | Type: HUMAN OTC DRUG LABEL
Date: 20231010

ACTIVE INGREDIENTS: BAPTISIA TINCTORIA ROOT 3 [hp_X]/1 mL; ECHINACEA ANGUSTIFOLIA WHOLE 3 [hp_X]/1 mL; PHYTOLACCA AMERICANA ROOT 6 [hp_X]/1 mL; ACONITUM NAPELLUS WHOLE 12 [hp_X]/1 mL; ARSENIC TRIOXIDE 12 [hp_X]/1 mL; ATROPA BELLADONNA 12 [hp_X]/1 mL; FERROSOFERRIC PHOSPHATE 12 [hp_X]/1 mL; LACHESIS MUTA VENOM 12 [hp_X]/1 mL; MERCURIC CHLORIDE 12 [hp_X]/1 mL; PHOSPHORUS 12 [hp_X]/1 mL; ESCHERICHIA COLI 30 [hp_X]/1 mL; RANCID BEEF 30 [hp_X]/1 mL
INACTIVE INGREDIENTS: WATER; ALCOHOL

DRUG FACTS:

ACTIVE INGREDIENTS:

(in each drop): of Aconitum Napellus 12X, Arsenicum Album 12X, Belladonna 12X, Colibacillinum Cum Natrum Muriaticum 30X, Ferrum Phosphoricum 12X, Lachesis Mutus 12X, Mercurius Corrosivus 12X, Phosphorus 12X, Phytolacca Decandra 6X, Pyrogenium 30X; 0.10% of Baptisia Tinctoria 3X, Echinacea 3X.

PURPOSE:

May temporarily relieve fever, irritated throat, and acute irritation of the bladder.**
**Claims based on traditional homeopathic practice, not accepted medical evidence. Not FDA evaluated.

WARNINGS:

If pregnant or breast-feeding, ask a health professional before use.

Keep out of reach of children. In case of overdose, get medical help or contact a Poison Control Center right away.

Do not use if tamper evident seal is broken or missing.

Store in a cool, dry place.

Warning: Severe or persistent sore throat or sore throat accompanied by high fever, headache, nausea, and vomiting may be serious. Consult physician promptly. Do not use more than 2 days or administer to children under 3 years of age unless directed by a physician.

KEEP OUT OF REACH OF CHILDREN:

In case of overdose, get medical help or contact a Poison Control Center right away.

DIRECTIONS:

Adults and children 5 to 10 drops orally, 3 times daily or as otherwise directed by a health care professional. If symptoms persist for more than 2 days, consult your health care professional. Consult a physician for use in children under 12 years of age.

INDICATIONS:

May temporarily relieve fever, irritated throat, and acute irritation of the bladder.**
**Claims based on traditional homeopathic practice, not accepted medical evidence. Not FDA evaluated.

INACTIVE INGREDIENTS:

Demineralized water, 20% Ethanol.

QUESTIONS:

Dist. by Energique, Inc.

201 Apple Blvd.

Woodbine, IA 51579 800.869.8078

PACKAGE LABEL DISPLAY:

ENERGIQUE

SINCE 1987

HOMEOPATHIC REMEDY

LYMPHASTAT B™

2 fl. oz. (60 ml)